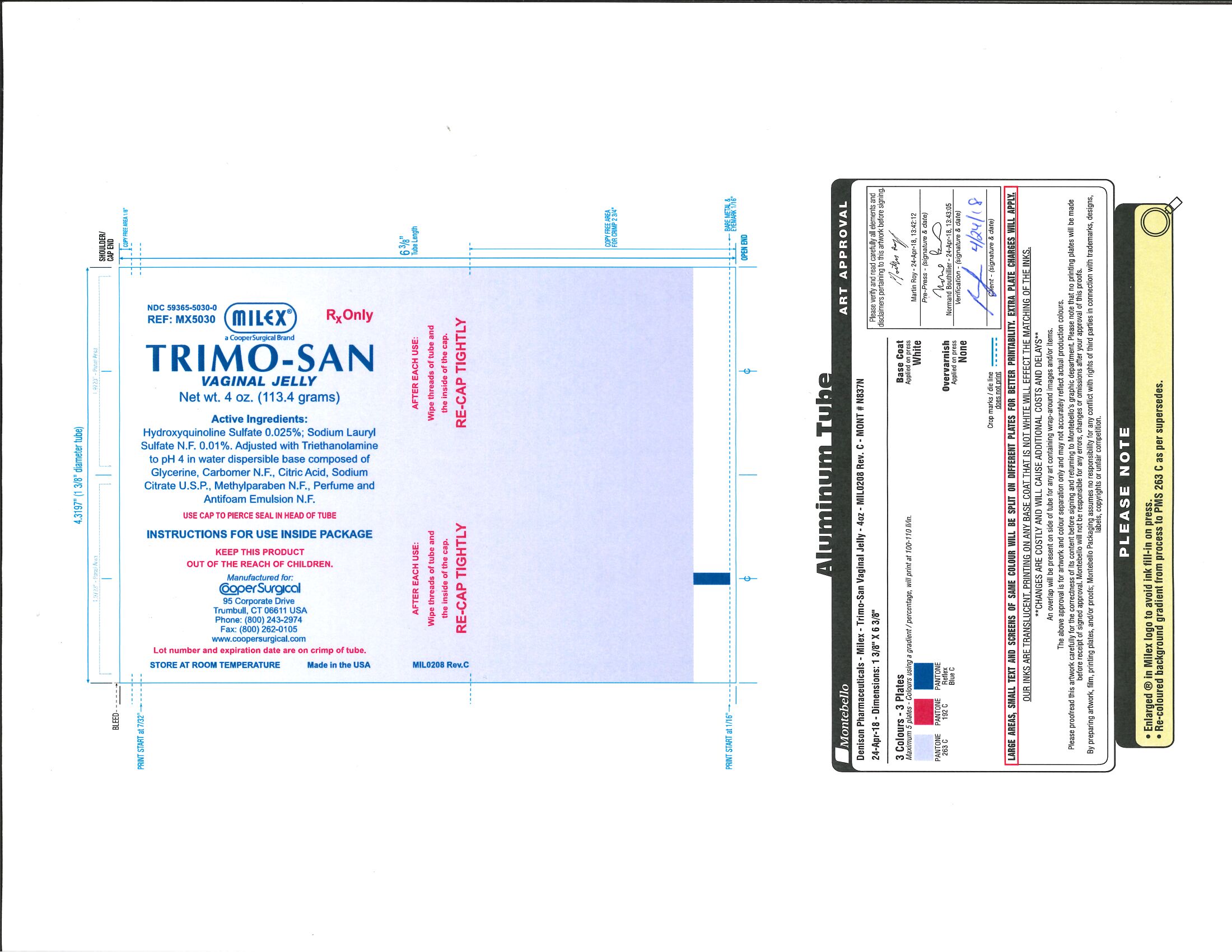 DRUG LABEL: Trimo-San
NDC: 0295-5030 | Form: JELLY
Manufacturer: Denison Pharmaceuticals, LLC
Category: prescription | Type: HUMAN PRESCRIPTION DRUG LABEL
Date: 20190911

ACTIVE INGREDIENTS: OXYQUINOLINE SULFATE 0.25 mg/1 g; SODIUM LAURYL SULFATE 0.1 mg/1 g
INACTIVE INGREDIENTS: CITRIC ACID MONOHYDRATE; METHYLPARABEN; TROLAMINE; SODIUM CITRATE; CARBOMER 934; WATER

Trimo San

CONTENTS

Hydroxyquinoline Sulfate 0.025%; Sodium Lauryl Sulfate N.F. 0.01%. Adjusted with Triethanolamine to pH 4 in water dispersible base composed of Glycerine, Carbomer N.F., Citric Acid, Sodium Citrate U.S.P., Methylparaben N.F., Perfume and Antifoam Emulsion N.F.

STORAGE:

AFTER EACH USE Wipe threads of tube and the inside of the cap. RE-CAP TIGHTLY. Store at room temperature.

TRIMO-SAN and PREGNANCY

TRIMO-SAN has NOT been tested for use during pregnancy.

- CooperSurgical does not recommend the use of TRIMO-SAN during pregnancy.
- If you wish to become pregnant, do not use TRIMO-SAN or any other personal hygiene product vaginally (douches, vaginal sprays, jellies or suppositories), for 6 hours prior to or following intercourse. Any product used within this time period could interfere with conception.

GENERAL INFORMATION

Use Cap to pierce seal in head of tube

Instructions for use inside package

Keep this product out of the reach of children